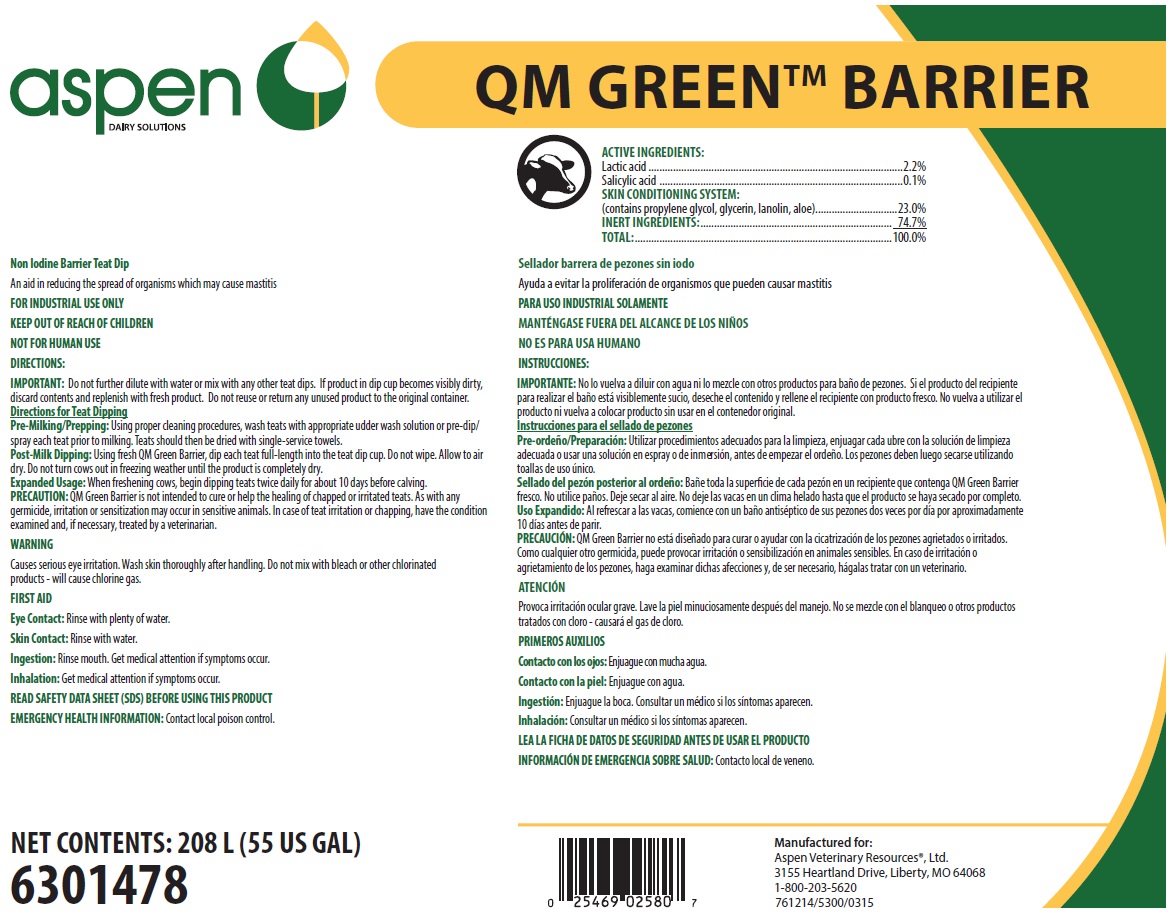 DRUG LABEL: QM Green Barrier
NDC: 46066-401 | Form: SOLUTION
Manufacturer: Aspen Veterinary Resources
Category: animal | Type: OTC ANIMAL DRUG LABEL
Date: 20250626

ACTIVE INGREDIENTS: LACTIC ACID 22 mg/1 mL; SALICYLIC ACID 1 mg/1 mL
INACTIVE INGREDIENTS: PROPYLENE GLYCOL; GLYCERIN; LANOLIN; ALOE; WATER

SAFE HANDLING WARNING

FOR INDUSTRIAL USE ONLY

KEEP OUT OF REACH OF CHILDREN

NOT FOR HUMAN USE

WARNING

Causes serious eye irritation. Wash skin thoroughly after handling. Do not mix with bleach or other chlorinated products - will cause chlorine gas.

DIRECTIONS:

IMPORTANT: Do not further dilute with water or mix with any other teat dips. If product in dip cup becomes visibly dirty, discard contents and replenish with fresh product. Do not reuse or return any unused product to the original container. Directions for Teat Dipping

Pre-Milking/Prepping: Using proper cleaning procedures, wash teats with appropriate udder wash solution or pre-dip/spray each teat prior to milking. Teats should then be dried with single-service towels.

Post-Milk Dipping: Using fresh QM Green Barrier, dip each teat full-length into the teat dip cup. Do not wipe. Allow to air dry. Do not turn cows out in freezing weather until the product is completely dry.

Expanded Usage: When freshening cows, begin dipping teats twice daily for about 10 days before calving.

PRECAUTION: QM Green Barrier is not intended to cure or help the healing of chapped or irritated teats. As with any germicide, irritation or sensitization may occur in sensitive animals. In case of teat irritation or chapping, have the condition examined and, if necessary, treated by a veterinarian.

OTHER SAFETY INFORMATION

FIRST AID

Eye Contact: Rinse with plenty of water.

Skin Contact: Rinse with water.

Ingestion: Rinse mouth. Get medical attention if symptoms occur.

Inhalation: Get medical attention if symptoms occur.

READ SAFETY DATA SHEET (SDS) BEFORE USING THIS PRODUCT

EMERGENCY HEALTH INFORMATION: Contact local poison control.

Principal display panel and representative label

aspen DIARY SOLUTIONS

QM GREEN BARRIER

Non iodine Barrier Teat Dip

An aid in reducing the spread of organisms which may cause mastitis

ACTIVE INGREDIENTS:

Lactic Acid..............................................................2.2%

Salicylic acid...........................................................0.1%

SKIN CONDITIONING SYSTEM:

(contains propylene glycol, glycerin, lanolin, aloe).....23.0%

INERT INGREDIENTS:...........................................74.7%

TOTAL:...............................................................100.0%

NET CONTENTS: 208 L (55 US GAL)

6301478

Manufactured for:

Aspen Veterinary Resources®, Ltd.

3155 Heartland Drive, Liberty, MO 64068

1-800-203-5620

761214/5300/0315